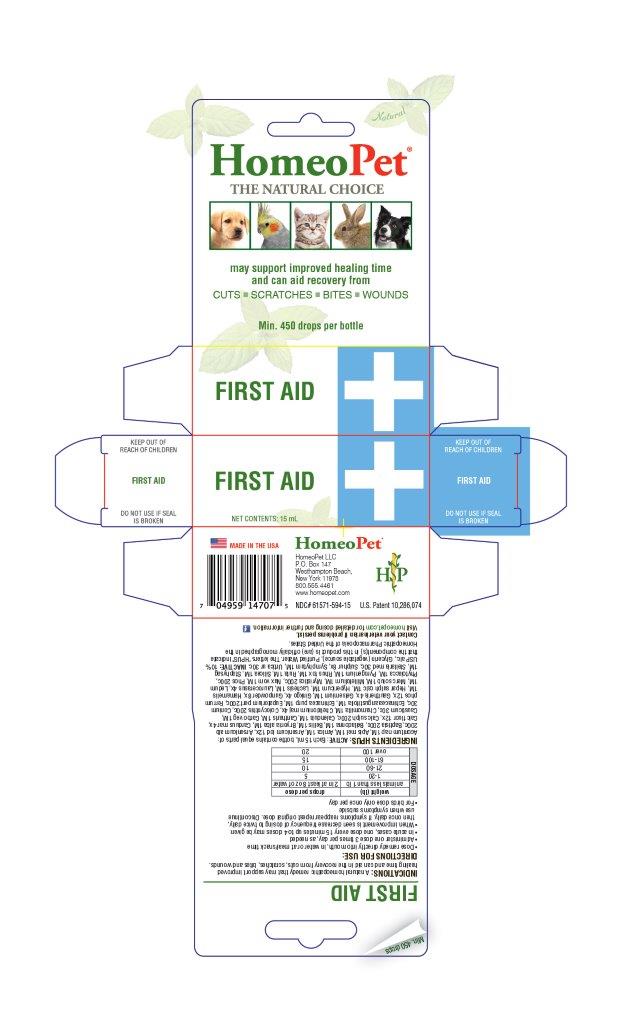 DRUG LABEL: First Aid
NDC: 61571-594 | Form: LIQUID
Manufacturer: HomeoPet, LLC
Category: homeopathic | Type: OTC ANIMAL DRUG LABEL
Date: 20201220

ACTIVE INGREDIENTS: ACONITUM NAPELLUS 1 [hp_M]/15 mL; APIS MELLIFERA 1 [hp_M]/15 mL; ARNICA MONTANA 1 [hp_M]/15 mL; ARSENIC TRIIODIDE 12 [hp_X]/15 mL; ARSENIC TRIOXIDE 200 [hp_C]/15 mL; BAPTISIA TINCTORIA ROOT 200 [hp_C]/15 mL; ATROPA BELLADONNA 1 [hp_M]/15 mL; BELLIS PERENNIS 1 [hp_M]/15 mL; BRYONIA ALBA ROOT 1 [hp_M]/15 mL; MILK THISTLE 4 [hp_X]/15 mL; CALCIUM FLUORIDE 12 [hp_X]/15 mL; CALCIUM SULFATE ANHYDROUS 200 [hp_C]/15 mL; CALENDULA OFFICINALIS FLOWER 1 [hp_M]/15 mL; LYTTA VESICATORIA 1 [hp_M]/15 mL; ACTIVATED CHARCOAL 1 [hp_M]/15 mL; CAUSTICUM 30 [hp_C]/15 mL; MATRICARIA CHAMOMILLA FLOWERING TOP 1 [hp_M]/15 mL; CHELIDONIUM MAJUS 4 [hp_X]/15 mL; CITRULLUS COLOCYNTHIS FRUIT PULP 200 [hp_C]/15 mL; CONIUM MACULATUM FLOWERING TOP 30 [hp_C]/15 mL; ECHINACEA ANGUSTIFOLIA 1 [hp_M]/15 mL; ECHINACEA PURPUREA 1 [hp_M]/15 mL; EUPATORIUM PERFOLIATUM FLOWERING TOP 200 [hp_C]/15 mL; FERROSOFERRIC PHOSPHATE 12 [hp_X]/15 mL; GAULTHERIA PROCUMBENS TOP 4 [hp_X]/15 mL; GELSEMIUM SEMPERVIRENS ROOT 1 [hp_M]/15 mL; GINKGO 4 [hp_X]/15 mL; POTASSIUM NITRATE 8 [hp_X]/15 mL; HAMAMELIS VIRGINIANA ROOT BARK/STEM BARK 1 [hp_M]/15 mL; CALCIUM SULFIDE 1 [hp_M]/15 mL; HYPERICUM PERFORATUM 1 [hp_M]/15 mL; LACHESIS MUTA VENOM 1 [hp_M]/15 mL; PRUNUS LAUROCERASUS LEAF 4 [hp_X]/15 mL; RHODODENDRON TOMENTOSUM LEAFY TWIG 1 [hp_M]/15 mL; MERCURIUS SOLUBILIS 1 [hp_M]/15 mL; ACHILLEA MILLEFOLIUM 1 [hp_M]/15 mL; VIROLA SEBIFERA RESIN 200 [hp_C]/15 mL; STRYCHNOS NUX-VOMICA SEED 1 [hp_M]/15 mL; PHOSPHORUS 200 [hp_Q]/15 mL; PHYTOLACCA AMERICANA ROOT 1 [hp_M]/15 mL; RANCID BEEF 1 [hp_M]/15 mL; TOXICODENDRON PUBESCENS LEAF 1 [hp_M]/15 mL; RUTA GRAVEOLENS FLOWERING TOP 1 [hp_M]/15 mL; SILICON DIOXIDE 1 [hp_M]/15 mL; DELPHINIUM STAPHISAGRIA SEED 1 [hp_M]/15 mL; STELLARIA MEDIA 30 [hp_C]/15 mL; SULFUR 8 [hp_X]/15 mL; COMFREY ROOT 1 [hp_M]/15 mL; URTICA URENS 30 [hp_C]/15 mL
INACTIVE INGREDIENTS: ALCOHOL; GLYCERIN; WATER

First Aid

PURPOSE

May support improved healing time and can aid recovery from

CUTS-SCRATCHES-BITES-WOUNDS

DOSAGE:

weight (lb) | drops per dose
animals less than 1 lb | 2 in at least 8 oz of water
1-20 | 5
21-60 | 10
61-100 | 15
over 100 | 20

ASK DOCTOR

Contact Veterinarian if problems persist.

Visit homeopet.com for detailed dosing and further information.

ACTIVE INGREDIENT

INGREDIENTS HPUS: ACTIVE: Each 15mL contains equal parts of: Aconitum nap 1M, Apis mel 1M, Arnica 1M, Arsenicum iod 12x, Arsenicum alb 200c, Baptisia 200c, Belladonna 1M, Bellis 1M, Bryonia alba 1M, Carduus mar 4x, Calc fluor 12x, Calc sulph 200c, Calendula 1M, Cantharis 1M, Carbo veg 1M, Causticum 30c, Chamomilla 1M, Chelidonium maj 4x, Colocynthis 200c, Conium 30c, Echinacea angustifolia 1M, Echinacea purp 1M, Eupatorium perf 200c, Ferrum phos 12x, Gaultheria 4x, Gelsemium 1M, Ginkgo 4x, Gunpowder 8x, Hamamelis 1M, Hepar sulph calc 1M, Hypericum 1M, Lachesis 1M, Laurocerasus 4x, Ledum 1M, Merc solub 1M, Millefolium 1M, Myristica 200c, Nux vom 1M, Phos 200c, Phytolacca 1M, Pyrogenium 1M, Rhus tox 1M, Ruta 1M, Silicea 1M, Staphysag 1M, Stellaria med 30c, Sulphur 8x, Symphytum 1M, Urtica ur 30c.

INACTIVE INGREDIENT

Alcohol, Glycerin, Purified Water